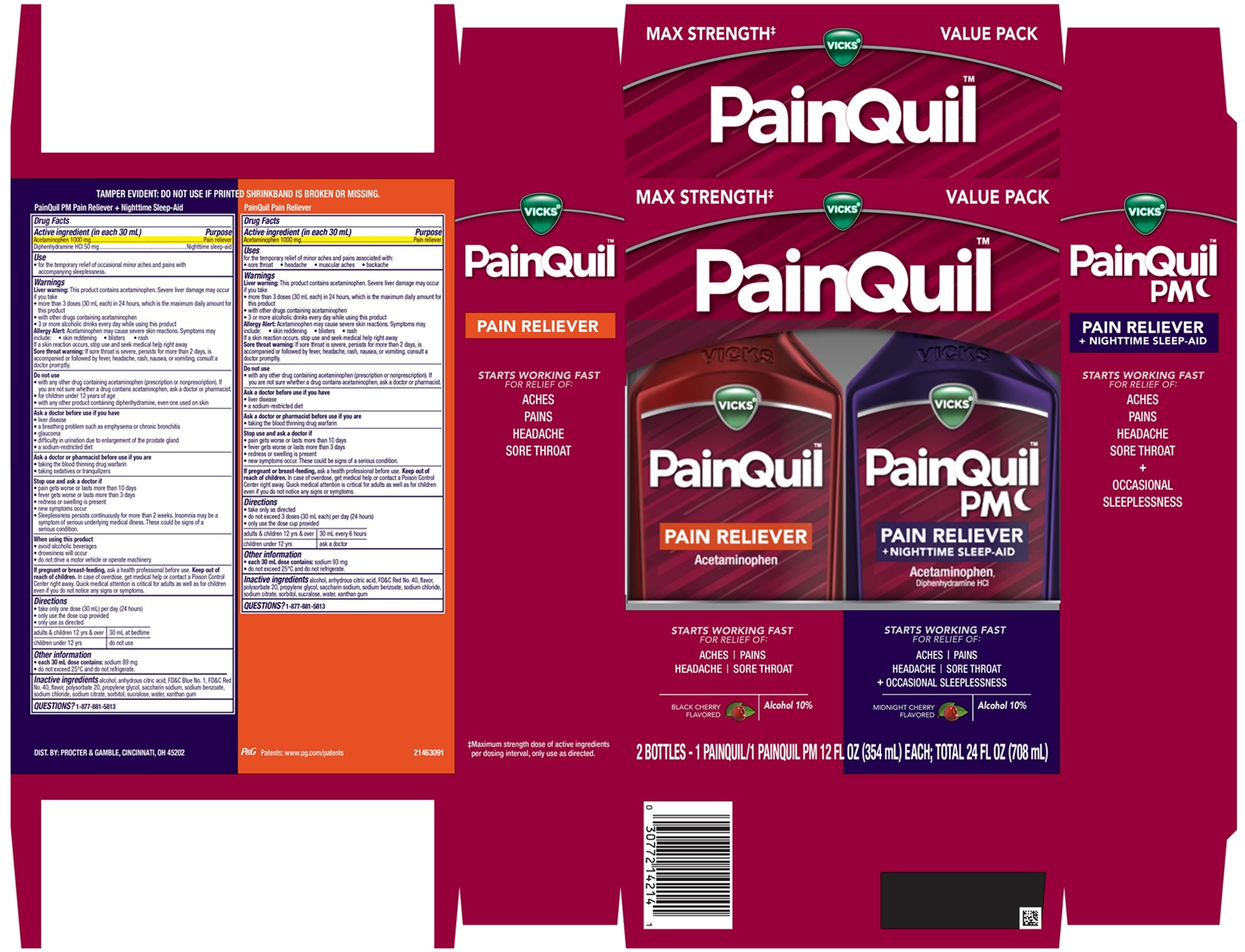 DRUG LABEL: Vicks PainQuil and Vicks PainQuil PM
NDC: 69423-849 | Form: KIT | Route: ORAL
Manufacturer: The Procter & Gamble Manufacturing Company
Category: otc | Type: HUMAN OTC DRUG LABEL
Date: 20251201

ACTIVE INGREDIENTS: ACETAMINOPHEN 1000 mg/30 mL; ACETAMINOPHEN 1000 mg/30 mL; DIPHENHYDRAMINE HYDROCHLORIDE 50 mg/30 mL; ACETAMINOPHEN 1000 mg/30 mL; DIPHENHYDRAMINE HYDROCHLORIDE 50 mg/30 mL
INACTIVE INGREDIENTS: ALCOHOL; PROPYLENE GLYCOL; POLYSORBATE 20; SACCHARIN SODIUM; ANHYDROUS CITRIC ACID; WATER; TRISODIUM CITRATE DIHYDRATE; FD&C RED NO. 40; SODIUM BENZOATE; SODIUM CHLORIDE; SORBITOL; SUCRALOSE; XANTHAN GUM; ANHYDROUS CITRIC ACID; POLYSORBATE 20; SACCHARIN SODIUM; WATER; FD&C RED NO. 40; FD&C BLUE NO. 1; SODIUM BENZOATE; SODIUM CHLORIDE; SORBITOL; SUCRALOSE; TRISODIUM CITRATE DIHYDRATE; XANTHAN GUM; PROPYLENE GLYCOL; ALCOHOL; ANHYDROUS CITRIC ACID; POLYSORBATE 20; SACCHARIN SODIUM; WATER; FD&C RED NO. 40; FD&C BLUE NO. 1; SODIUM BENZOATE; SODIUM CHLORIDE; SORBITOL; SUCRALOSE; TRISODIUM CITRATE DIHYDRATE; XANTHAN GUM; PROPYLENE GLYCOL; ALCOHOL

Vicks® PainQuil™ / Vicks® PainQuil™ PM
PAIN RELIEVER Convenience Pack

Vicks ® PainQuil™ PM PAIN RELIEVER + NIGHTTIME SLEEP-AID

Drug Facts

Active ingredients (in each 30 mL)

Acetaminophen 1000 mg

Diphenhydramine HCl 50 mg

Purpose

Pain reliever

Nighttime sleep-aid

Uses

- for the temporary relief of occasional minor aches and pains with accompanying sleeplessness.

Warnings

Liver warning: This product contains acetaminophen. Severe liver damage may occur if you take

- more than 3 doses (30 mL each) in 24 hours, which is the maximum daily amount for this product
- with other drugs containing acetaminophen
- 3 or more alcoholic drinks every day while using this product

Allergy Alert: Acetaminophen may cause severe skin reactions.

Symptoms may include: • skin reddening • blisters • rash

If a skin reaction occurs, stop use and seek medical help right away

Sore throat warning: If sore throat is severe, persists for more than 2 days, is accompanied or followed by fever, headache, rash, nausea, or vomiting, consult a doctor promptly.

Do not use

- with any other drug containing acetaminophen (prescription or nonprescription). If you are not sure whether a drug contains acetaminophen, ask a doctor or pharmacist.
- for children under 12 years of age
- with any other product containing diphenhydramine, even one used on skin

Ask a doctor before use if you have

- liver disease
- a breathing problem such as emphysema or chronic bronchitis
- glaucoma
- difficulty in urination due to enlargement of the prostate gland
- a sodium-restricted diet

Ask a doctor or pharmacist before use if you are

- taking the blood thinning drug warfarin
- taking sedatives or tranquilizers

Stop use and ask a doctor if

- pain gets worse or lasts more than 10 days
- fever gets worse or lasts more than 3 days
- redness or swelling is present
- new symptoms occur
- sleeplessness persists continuously for more than 2 weeks.

Insomnia may be a symptom of serious underlying medical illness.

These could be signs of a serious condition.

When using this product

- avoid alcoholic beverages
- drowsiness will occur
- do not drive a motor vehicle or operate machinery

If pregnant or breast-feeding,

ask a health professional before use.

Keep out of reach of children.

OVERDOSAGE

In case of overdose, get medical help or contact a Poison Control Center right away. Quick medical attention is critical for adults as well as for children even if you do not notice any signs or symptoms.

Directions

- take only one dose (30 mL) per day (24 hours)
- only use the dose cup provided
- only use as directed

adults & children 12 yrs & over | 30 mL at bedtime
children under 12 yrs | do not use

Other information

- each 30 mL contains: sodium 89 mg
- do not exceed 25°C and do not refrigerate.

Inactive ingredients

alcohol, anhydrous citric acid, FD&C Blue No. 1, FD&C Red No. 40, flavor, polysorbate 20, propylene glycol, saccharin sodium, sodium benzoate, sodium chloride, sodium citrate, sorbitol, sucralose, water, xanthan gum

Questions?

1-877-881-5813

TAMPER EVIDENT: DO NOT USE IF PRINTED SHRINKBAND IS BROKEN OR MISSING.

DIST. BY: PROCTER & GAMBLE,

CINCINNATI, OH 45202

Vicks ® PainQuil™ PAIN RELIEVER

Drug Facts

Active ingredients (in each 30 mL)

Acetaminophen 1000 mg

Purpose

Pain reliever

Uses

for the temporary relief of minor aches and pains associated with:

- sore throat
- headache
- muscular aches
- backache

Warnings

Liver warning: This product contains acetaminophen. Severe liver damage may occur if you take

- more than 3 doses (30 mL each) in 24 hours, which is the maximum daily amount for this product
- with other drugs containing acetaminophen
- 3 or more alcoholic drinks every day while using this product

Allergy Alert: Acetaminophen may cause severe skin reactions.

Symptoms may include: • skin reddening • blisters • rash

If a skin reaction occurs, stop use and seek medical help right away

Sore throat warning: If sore throat is severe, persists for more than 2 days, is accompanied or followed by fever, headache, rash, nausea, or vomiting, consult a doctor promptly.

Do not use

- with any other drug containing acetaminophen (prescription or nonprescription). If you are not sure whether a drug contains acetaminophen, ask a doctor or pharmacist.

Ask a doctor before use if you have

- liver disease
- a sodium-restricted diet

Ask a doctor or pharmacist before use if you are

- taking the blood thinning drug warfarin

Stop use and ask a doctor if

- pain gets worse or lasts more than 10 days
- fever gets worse or lasts more than 3 days
- redness or swelling is present
- new symptoms occur.

These could be signs of a serious condition.

PREGNANCY OR BREAST FEEDING

If pregnant or breast-feeding,ask a health professional before use.

Keep out of reach of children.

OVERDOSAGE

In case of overdose, get medical help or contact a Poison Control Center right away. Quick medical attention is critical for adults as well as for children even if you do not notice any signs or symptoms.

Directions

- take only as directed
- do not exceed 3 doses (30 mL each) per day (24 hours)
- only use the dose cup provided

adults & children 12 yrs & over | 30 mL every 6 hours
children under 12 yrs | do not use

Other information

- each 30 mL contains: sodium 93 mg
- do not exceed 25°C and do not refrigerate.

Inactive ingredients

alcohol, anhydrous citric acid, FD&C Red No. 40, flavor, polysorbate 20, propylene glycol, saccharin sodium, sodium benzoate, sodium chloride, sodium citrate, sorbitol, sucralose, water, xanthan gum

Questions?

1-877-881-5813

TAMPER EVIDENT: DO NOT USE IF PRINTED SHRINKBAND IS BROKEN OR MISSING.

DIST. BY: PROCTER & GAMBLE,

CINCINNATI, OH 45202

PRINCIPAL DISPLAY PANEL - Convenience Pack

Vicks®PainQuil™ PAIN RELIEVER / Vicks®PainQuil™ PM PAIN RELIEVER + NIGHTTIME SLEEP-AID
MAX STRENGTH‡

VALUE PACK

‡Maximum strength dose of active ingredients per dosing interval, only use as directed.

Vicks®PainQuil™ PAIN RELIEVER

STARTS WORKING FAST FOR RELIEF OF:

ACHES

PAINS

HEADACHE

SORE THROAT

BLACK CHERRY FLAVORED

Alcohol 10%

Vicks®PainQuil™ PM PAIN RELIEVER + NIGHTTIME SLEEP-AID

STARTS WORKING FAST FOR RELIEF OF:

ACHES

PAINS

HEADACHE

SORE THROAT

+

OCCASSIONAL SLEEPLESSNESS

MIDNIGHT CHERRY FLAVORED

Alcohol 10%

2 BOTTLES - 1 PAINQUIL/1 PAINQUIL PM 12 FL OZ (354 mL) EACH; TOTAL 24 FL OZ (708 mL)